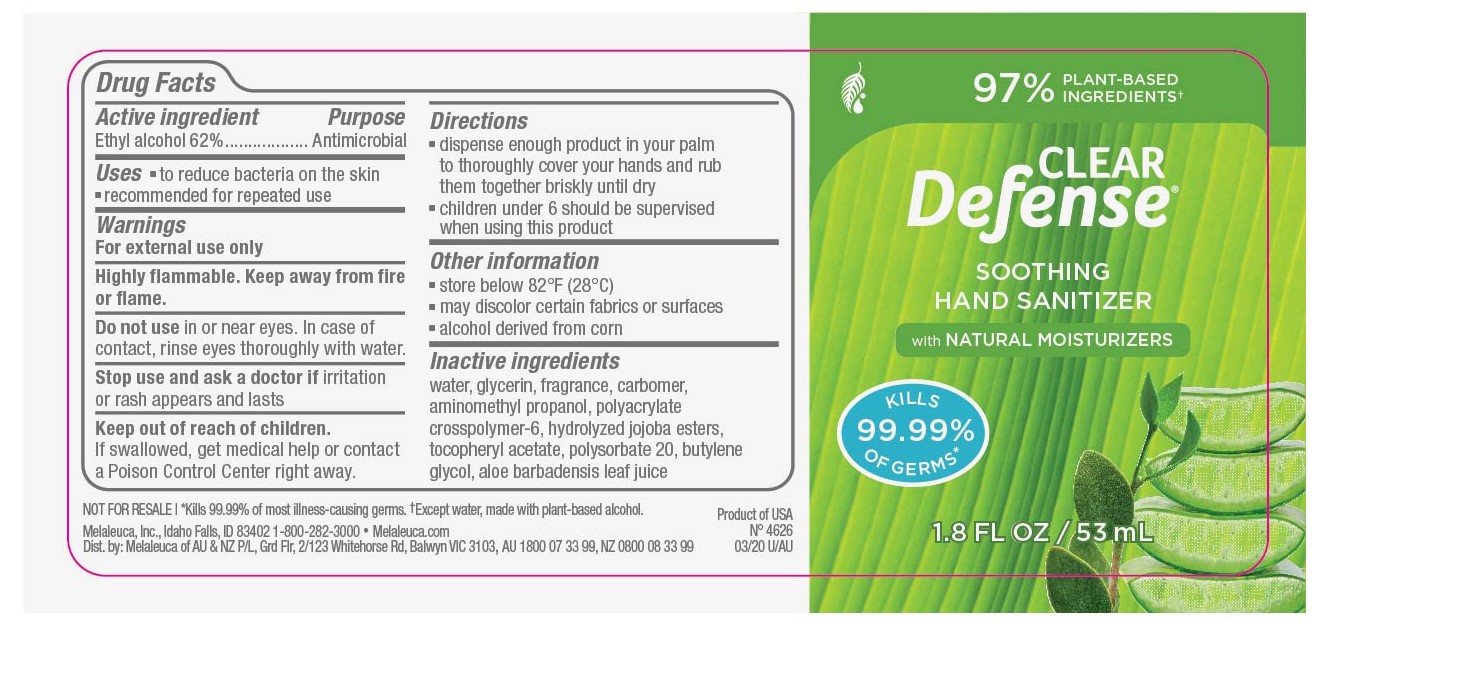 DRUG LABEL: Clear Defense
NDC: 54473-311 | Form: GEL
Manufacturer: Melaleuca, Inc.
Category: otc | Type: HUMAN OTC DRUG LABEL
Date: 20250402

ACTIVE INGREDIENTS: ALCOHOL 150.97 g/266 mL
INACTIVE INGREDIENTS: WATER; GLYCERIN; ALOE VERA LEAF; POLYSORBATE 20; ALPHA-TOCOPHEROL ACETATE; CARBOMER HOMOPOLYMER, UNSPECIFIED TYPE; AMMONIUM ACRYLOYLDIMETHYLTAURATE, DIMETHYLACRYLAMIDE, LAURYL METHACRYLATE AND LAURETH-4 METHACRYLATE COPOLYMER, TRIMETHYLOLPROPANE TRIACRYLATE CROSSLINKED (45000 MPA.S); BUTYLENE GLYCOL; HYDROLYZED JOJOBA ESTERS (ACID FORM); AMINOMETHYLPROPANOL

Clear Defense Hand Gel

Active ingredient
Ethyl Alcohol 62%

Purpose
Antimicrobial

Uses

- to reduce bacteria on the skin
- recommended for repeated use

Warnings
For External use only
Highly flammable. Keep away from fire or flame.

Do not use in or near eyes. In case of contact, rinse eyes thoroughly with water.

Stop use and ask a doctor if irritation or rash appears and lasts.

Keep out of reach of children. If swallowed, get medical help or contact a Poison Control Center right away.

Directions

- dispense a generous amount of gel in your palm
- spread gel over your hands until thoroughly coated
- rub your hands together briskly until dry
- children under 6 should be supervised when using this product

Other information

- store below 82°F (28°C)

Other information

- may discolor certain fabrics or surfaces

Inactive ingredients
water, glycerin, xylitol, anhydroxylitol, xylitylglucoside, carbomer, aminomethyl propanol, fragrance, aloe barbadensis leaf extract, melaleuca alternifolia (tea tree) leaf oil, polysorbate 20, tocopheryl acetate